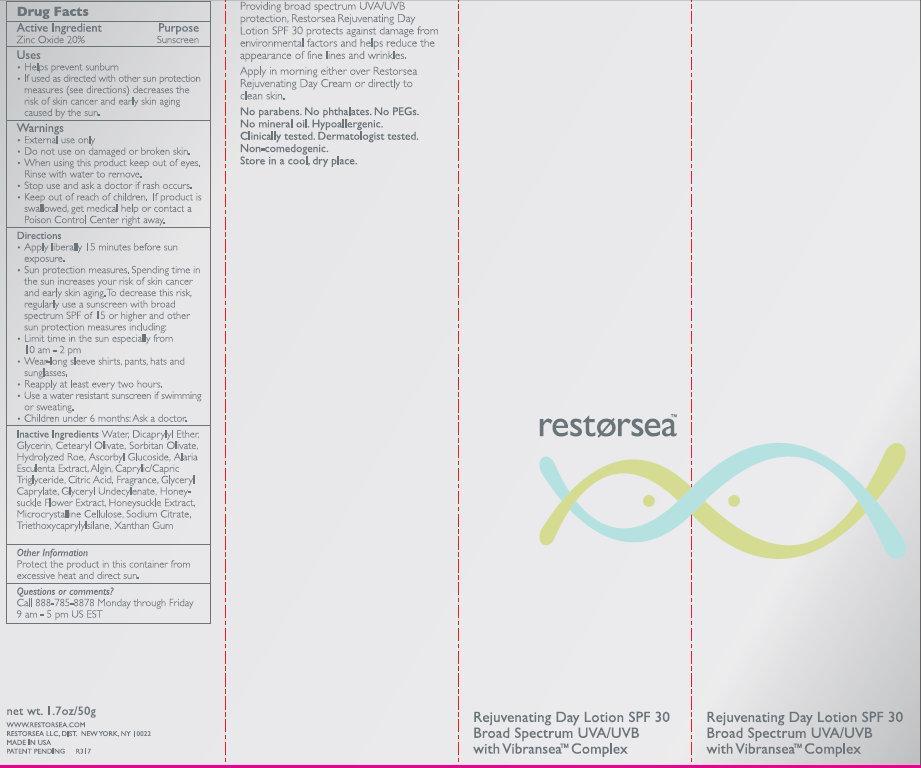 DRUG LABEL: restorsea Rejuvenating Day SPF 30 Broad Spectrum UVA UVB with Vibransea Complex
NDC: 57670-000 | Form: LOTION
Manufacturer: RESTORSEA INC
Category: otc | Type: HUMAN OTC DRUG LABEL
Date: 20231212

ACTIVE INGREDIENTS: ZINC OXIDE 20 g/100 g
INACTIVE INGREDIENTS: WATER; DICAPRYLYL ETHER; GLYCERIN; CETEARYL OLIVATE; SORBITAN OLIVATE; ASCORBYL GLUCOSIDE; ALARIA ESCULENTA; MEDIUM-CHAIN TRIGLYCERIDES; CITRIC ACID MONOHYDRATE; GLYCERYL CAPRYLATE; LONICERA CAPRIFOLIUM FLOWER; CELLULOSE, MICROCRYSTALLINE; SODIUM CITRATE; TRIETHOXYCAPRYLYLSILANE; XANTHAN GUM

restorsea Rejuvenating Day Lotion SPF 30 Broad Spectrum UVA/UVB with Vibransea Complex

Active Ingredient

Zinc Oxide 20%

Purpose

Sunscreen

Uses

- Helps prevent sunburn
- If used as directed with other sun protection measures (see directions) decreases the risk of skin cancer and early skin aging caused by the sun.

Warnings

- For external use only

Do not use

on damaged or broken skin

When using this product

keep out of eyes. Rinse with water to remove.

Stop use and ask a doctor

if rash occurs.

Keep out of reach of children.

If product is swallowed, get medical help or contact a Poison Control Center right away.

Directions

- Apply liberally 15 minutes before sun exposure.
- Sun protection measures. Spending time in the sun increases your risk of skin cancer and early skin aging. To decrease this risk, regularly use a sunscreen with broad spectrum SPF 15 or higher and other sun protection measures including:
- Limit time in the sun especially from 10 am - 2 pm
- Wear long sleeve shirts, pants, hats and sunglasses
- Reapply at least every two hours.
- Use a water resistant sunscreen if swimming or sweating.
- Children under 6 months: Ask a doctor.

Inactive Ingredients

Water, Dicaprylyl Ether, Glycerin, Cetearyl Olivate, Sorbitan Olivate, Hydrolyzed Roe, Ascorbyl Glucoside, Alaria Esculenta Extract, Algin, Caprylic/Capric Triglyceride, Citric Acid, Fragrance, Glyceryl Caprylate, Glyceryl Undecylenate, Honeysuckle Flower Extract, Honeysuckle Extract, Microcrystalline Cellulose, Sodium Citrate, Triethoxycapryl silane, Xanthan Gum

Other Information

Protect the product in this container from excessive heat and direct sun.

Questions or comments?

Call 888-785-8878 Monday through Friday 9 am - 5pm US EST

DESCRIPTION

Providing broad spectrum UVA/UVB protection, Restorsea Rejuvenating Day Lotion SPF 30 protects against damage from environmental factors and helps reduce the appearance of fine lines and wrinkles.

Apply in morning either over Restorsea Rejuvenating Day Cream or directly to clean skin.

No Parabens. No phthalates. No PEGs. No mineral oil. Hypoallergenic. Clinically tested. Dermatologist tested. Non-comedogenic. Store in a cool, dry place.

PACKAGE LABEL

restorsea Rejuvenating Day Lotion SPF 30 Broad Spectrum UVA/UVB with Vibransea Complex net wt. 1.7 oz / 50g www.restorsea.com RESTORSEA LLC, DIST. NEW YORK, NY 10022 MADE IN USA PATENT PENDINGTM